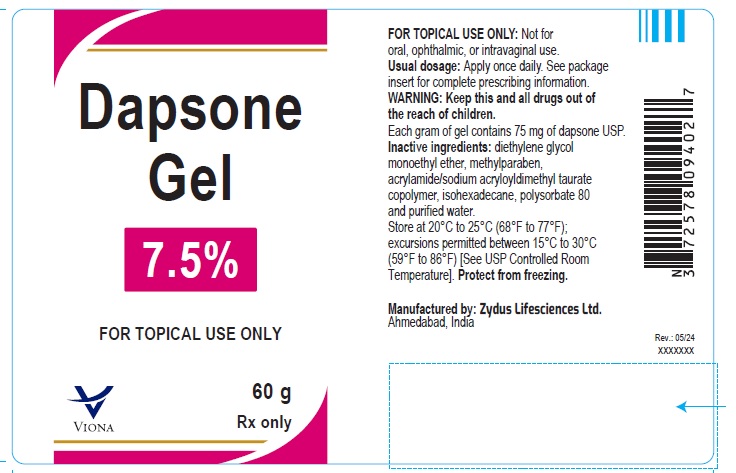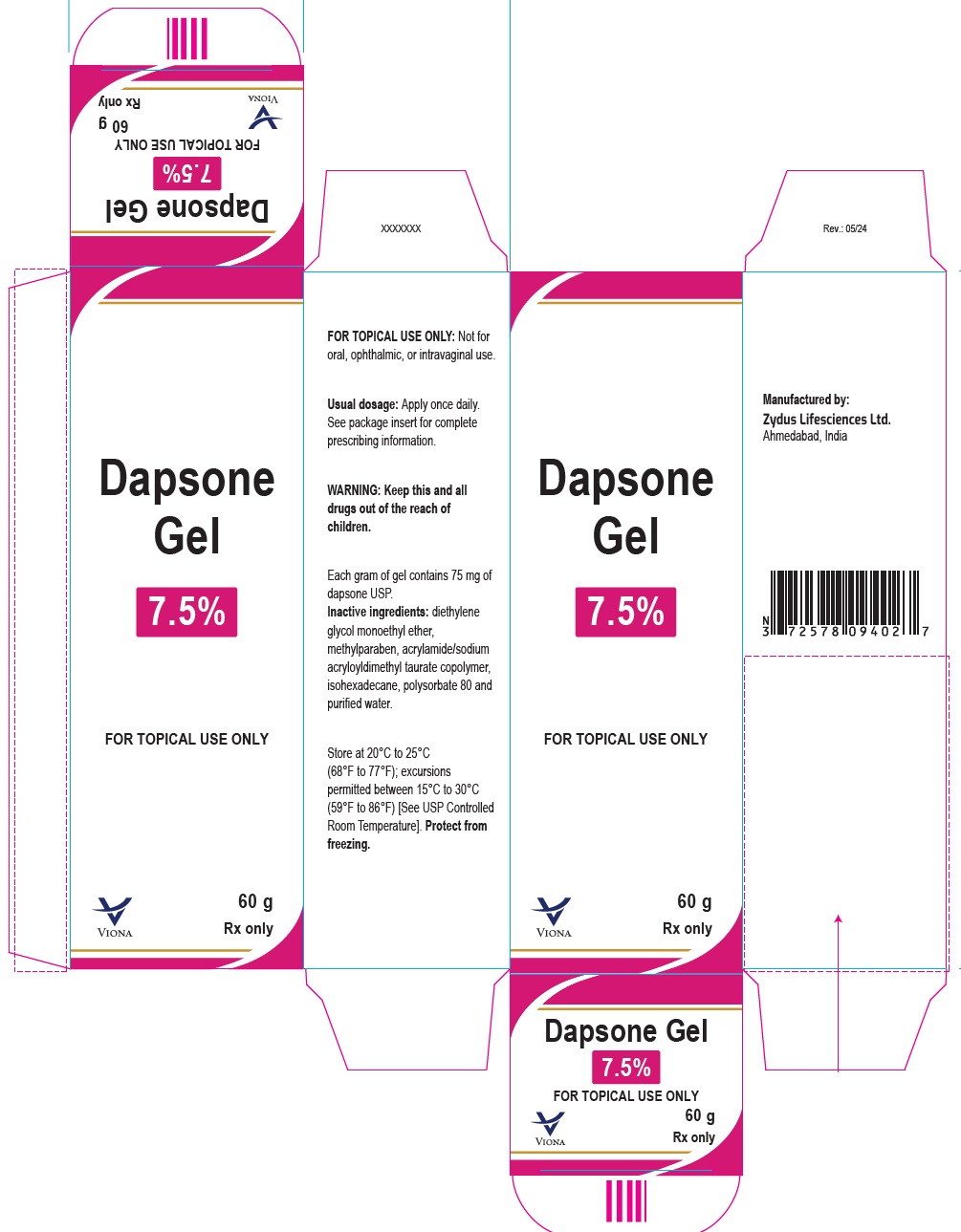 DRUG LABEL: Dapsone
NDC: 70771-1538 | Form: GEL
Manufacturer: Zydus Lifesciences Limited
Category: prescription | Type: HUMAN PRESCRIPTION DRUG LABEL
Date: 20240509

ACTIVE INGREDIENTS: DAPSONE 75 mg/1 g
INACTIVE INGREDIENTS: ACRYLAMIDE; DIETHYLENE GLYCOL MONOETHYL ETHER; ISOHEXADECANE; METHYLPARABEN; POLYSORBATE 80; SODIUM ACRYLOYLDIMETHYLTAURATE; WATER

Dapsone Gel

PACKAGE LABEL.PRINCIPAL DISPLAY PANEL

Dapsone Gel, 7.5%

60 g

NDC 70771-1538-3

Zydus

Rx only